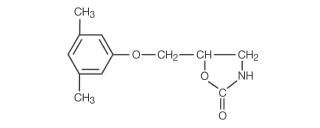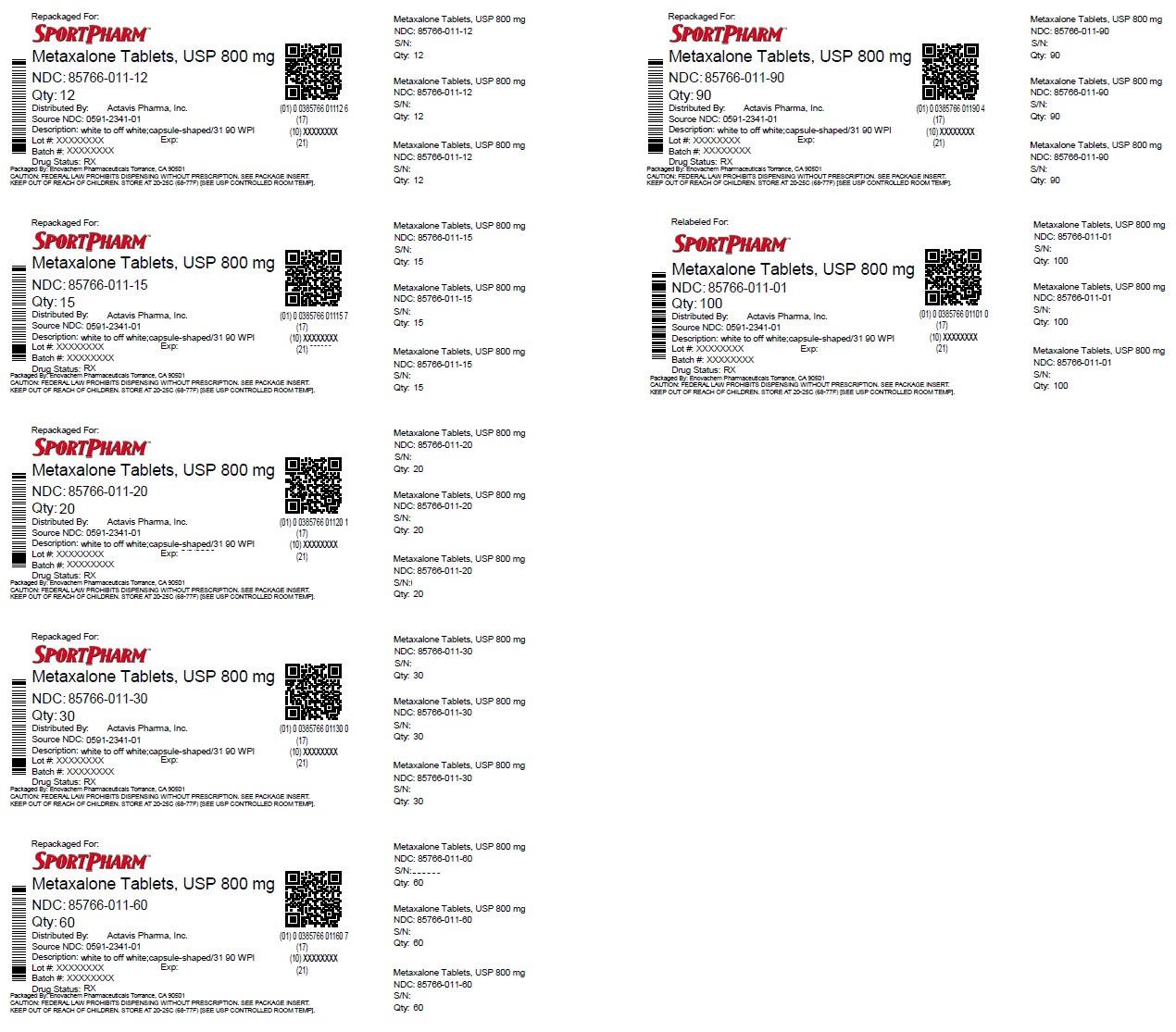 DRUG LABEL: Metaxalone
NDC: 85766-011 | Form: TABLET
Manufacturer: Sportpharm LLC
Category: prescription | Type: HUMAN PRESCRIPTION DRUG LABEL
Date: 20260203

ACTIVE INGREDIENTS: METAXALONE 800 mg/1 1
INACTIVE INGREDIENTS: ALGINIC ACID; AMMONIUM ALGINATE; CALCIUM ALGINATE; STARCH, CORN; MAGNESIUM STEARATE

HIGHLIGHTS OF PRESCRIBING INFORMATION

These highlights do not include all the information needed to use METAXALONE TABLETS safely and effectively. See full prescribing information for METAXALONE TABLETS.
METAXALONE tablets, for oral use
Initial U.S. Approval: 1962

RECENT MAJOR CHANGES

Dosage and Administration (2) 6/2024

1 INDICATIONS AND USAGE

Metaxalone tablets are a muscle relaxant indicated as an adjunct to rest, physical therapy, and other measures for the relief of discomforts associated with acute, painful musculoskeletal conditions in adults and pediatric patients 13 years of age and older. (1)

2 DOSAGE AND ADMINISTRATION

- Recommended dosage of metaxalone tablets in adults and pediatric patients 13 years of age and older is 800 mg orally three to four times a day. (2)
- Metaxalone tablets 800 mg are not substitutable on a mg to mg basis with metaxalone tablets, 640 mg. When it is appropriate to switch, see the Full Prescribing Information on switching instructions. (2)

3 DOSAGE FORMS AND STRENGTHS

Tablets: 800 mg capsule-shaped, scored white to off-white tablet, inscribed with “ 31 90” on the scored side and “ WPI” on the other side. (3)

4 CONTRAINDICATIONS

- Known hypersensitivity to any components of this product. (4)
- Known tendency to drug induced, hemolytic, or other anemias. (4)
- Severe renal or hepatic impairment. (4)

5 WARNINGS AND PRECAUTIONS

- Serotonin Syndrome: Cases of serotonin syndrome, a potentially life-threatening condition, have been reported during concomitant use of metaxalone tablets (within the recommended dosage range) and other serotonergic drugs and with the use of metaxalone tablets as the only serotonergic drug taken at a dosage higher than the recommended dosage. If concomitant use is warranted, carefully observe the patient, particularly during treatment initiation and dosage increases. Discontinue metaxalone tablets if serotonin syndrome is suspected or it occurs. (5.1, 7.1)
- Central Nervous System (CNS) Depression: Metaxalone tablets may impair mental and/or physical abilities required for the performance of hazardous tasks, such as operating machinery or driving a motor vehicle, especially when used with other CNS depressants including alcohol. Follow patients closely for signs and symptoms of respiratory depression and sedation. If concomitant use is warranted, closely monitor for signs of respiratory depression and sedation, particularly during treatment initiation and dosage increases. (5.2, 7.2)

6 ADVERSE REACTIONS

Most common adverse reactions (incidence >5%) are nausea and vomiting. (6)

To report SUSPECTED ADVERSE REACTIONS, contact Actavis at 1-888-838-2872 or FDA at 1-800-FDA-1088 or www.fda.gov/medwatch.

8 USE IN SPECIFIC POPULATIONS

Geriatric Use: Metaxalone tablets-treated geriatric patients may be especially susceptible to CNS depression. (8.5)

FULL PRESCRIBING INFORMATION

1 INDICATIONS AND USAGE

Metaxalone tablets are indicated as an adjunct to rest, physical therapy, and other measures for the relief of discomfort associated with acute, painful musculoskeletal conditions in adults and pediatric patients 13 years of age and older.

2 DOSAGE AND ADMINISTRATION

The recommended dosage of metaxalone tablets in adults and pediatric patients 13 years of age and older is 800 mg orally three to four times a day [see Use in Specific Populations (8)].

Metaxalone tablets 800 mg are not substitutable on a mg to mg basis with metaxalone tablets, 640 mg [see Clinical Pharmacology (12.3)]. When it is appropriate to switch:

- Switch only in patients who have been taking metaxalone tablets, 640 mg on an empty stomach.
- Stop metaxalone tablets, 640 mg three times a day and start metaxalone tablets 800 mg three times a day on an empty stomach, OR stop metaxalone tablets 640 mg four times a day and start metaxalone tablets 800 mg four times a day on an empty stomach.

Do not switch from metaxalone tablets, 640 mg to metaxalone tablets when the patient is taking food during administration.

3 DOSAGE FORMS AND STRENGTHS

Tablets: 800 mg capsule-shaped, scored white to off-white tablet, inscribed with “ 31 90” on the scored side and “ WPI” on the other side.

4 CONTRAINDICATIONS

Metaxalone tablets are contraindicated in patients with:

- Known hypersensitivity to any component of metaxalone tablets.
- Known tendency to drug induced, hemolytic, or other anemias.
- Severe renal or hepatic impairment.

5 WARNINGS AND PRECAUTIONS

5.1 Serotonin Syndrome

Cases of serotonin syndrome, a potentially life-threatening condition, have been reported during concomitant use of metaxalone tablets (within the recommended dosage range) and other serotonergic drugs [see Drug Interactions (7)] and with the use of metaxalone tablets as the only serotonergic drug taken at a dosage higher than the recommended dosage [see Overdosage (10)].

Serotonin syndrome symptoms may include mental status changes (e.g., agitation, hallucinations, coma), autonomic instability (e.g., tachycardia, labile blood pressure, hyperthermia), neuromuscular aberrations (e.g., hyperreflexia, incoordination, rigidity), and/or gastrointestinal symptoms (e.g., nausea, vomiting, diarrhea). The onset of symptoms generally occurs within several hours to a few days after initiation of a serotonergic drug, but may occur later than that.

If concomitant use of metaxalone tablets and another serotonergic drug is warranted, reassess the patient, particularly during treatment initiation and dosage increases. Discontinue metaxalone tablets if serotonin syndrome is suspected or it occurs.

5.2 Central Nervous System Depression

Because of its central nervous system (CNS) depressant effects, metaxalone tablets may impair mental and/or physical abilities required for performance of hazardous tasks, such as operating machinery or driving a motor vehicle, especially when used with other CNS depressants including alcohol. Geriatric patients may be especially susceptible to CNS depression associated with metaxalone tablets use. When used concomitantly, the sedative effects of metaxalone tablets and other CNS depressants (e.g., alcohol, benzodiazepines, opioids, tricyclic antidepressants) may be additive [see Drug Interactions (7)].

Follow metaxalone tablets-treated patients closely for signs and symptoms of respiratory depression and sedation. If concomitant use of metaxalone tablets and another CNS depressant is warranted, closely monitor for signs of respiratory depression and sedation, particularly during treatment initiation and dosage increases.

6 ADVERSE REACTIONS

The following adverse reactions associated with the use of metaxalone tablets were identified in clinical studies or postmarketing reports. Because some of these reactions were reported voluntarily from a population of uncertain size, it is not always possible to reliably estimate their frequency or establish a causal relationship to drug exposure. The most frequent reactions to metaxalone were:

- CNS: drowsiness, dizziness, headache, and nervousness or "irritability".
- Digestive: nausea, vomiting, gastrointestinal upset.
  Other adverse reactions were:
- CNS: cases of serotonin syndrome have been reported during concomitant use of metaxalone tablets (within the recommended dosage range) and other serotonergic drugs and with the use of metaxalone tablets as the only serotonergic drug at a dosage higher than the recommended dosage [see Warnings and Precautions (5.1), Drug Interactions (7.1) and Overdosage (10)].
- Hematologic: leukopenia; hemolytic anemia;
- Hepatobiliary: jaundice;
- Immune System: anaphylaxis, hypersensitivity reaction, rash with or without pruritus.

7 DRUG INTERACTIONS

7.1 Serotonergic Drugs

If concomitant use of metaxalone tablets and another serotonergic drug is warranted, carefully observe the patient, particularly during treatment initiation and dosage modification. Discontinue metaxalone tablets if serotonin syndrome is suspected or if it occurs.

Serotonin syndrome has resulted from concomitant use of metaxalone tablets (within the recommended dosage range) with other serotonergic drugs [see Warnings and Precautions (5.1) and Adverse Reactions (6)].

Serotonergic drugs include selective serotonin reuptake inhibitors (SSRIs), serotonin and norepinephrine reuptake inhibitors (SNRIs), tricyclic antidepressants (TCAs), triptans, 5-HT3 receptor antagonists, opioids (particularly fentanyl, meperidine, and methadone), drugs that affect the serotonergic neurotransmitter system (e.g., mirtazapine, trazodone, tramadol), and drugs that impair metabolism of serotonin (including monoamine oxidase (MAO) inhibitors, both those intended to treat psychiatric disorders and also others, such as linezolid and intravenous methylene blue).

7.2 CNS Depressants

If concomitant use of metaxalone tablets and another CNS depressant is warranted, closely monitor for signs of respiratory depression and sedation, particularly during treatment initiation and dosage increases.

Due to the additive pharmacologic effect, concomitant use of metaxalone tablets with other CNS depressants may increase the risk of sedation and respiratory depression [see Warnings and Precautions (5.2)].

7.3 Interaction of Metaxalone Tablets with Benedict’s Tests

False-positive Benedict's tests, due to an unknown reducing substance, have been noted in metaxalone tablets-treated patients. A glucose-specific test will differentiate findings.

8 USE IN SPECIFIC POPULATIONS

8.1 Pregnancy

Risk Summary

There are no available data on metaxalone tablets use in pregnant patients to evaluate for a drug-associated risk of major birth defects, miscarriage or other adverse maternal or fetal outcomes despite decades of metaxalone use. Reproduction studies in rats have not revealed effects on the fetus due to metaxalone.

The estimated background risk of major birth defects and miscarriage for the indicated population is unknown. All pregnancies have a background risk of birth defect, loss, or other adverse outcomes. In the U.S. general population, the estimated risk of major birth defects and miscarriage in clinically recognized pregnancies is 2 to 4% and 15 to 20%, respectively.

8.2 Lactation

Risk Summary

There are no data available to evaluate the presence of metaxalone or its metabolite in either human or animal milk, the effects on the breastfed infant, or the effects on milk production. The developmental and health benefits of breastfeeding should be considered along with the mother’s clinical need for metaxalone tablets and any potential adverse effects on the breastfed infant from metaxalone tablets or from the underlying maternal condition.

8.4 Pediatric Use

Metaxalone tablets are indicated as an adjunct to rest, physical therapy, and other measures for the relief of discomforts associated with acute, painful musculoskeletal conditions in pediatric patients 13 years of age and older. The safety and effectiveness of metaxalone tablets in pediatric patients 12 years of age or younger have not been established.

8.5 Geriatric Use

Clinical studies of metaxalone tablets did not include sufficient numbers of patients 65 years of age and older to determine whether they respond differently from younger adult patients.

Geriatric patients may be especially susceptible to CNS depression associated with metaxalone tablets use [see Warnings and Precautions (5.2)].

The recommended metaxalone tablets dosage in patients 65 years of age and older is the same as in younger adult patients. Metaxalone peak plasma concentrations (Cmax) and area under the curve (AUC) were higher in patients 65 years of age and older in the fasted state; however, a clinically significant difference was not observed when metaxalone was administered in the fed state [see Clinical Pharmacology (12.3)].

8.6 Hepatic Impairment

Metaxalone tablets are contraindicated in patients with severe hepatic impairment. Metaxalone tablets should be used with caution and additional follow-up should be considered in patients with mild to moderate hepatic impairment. The effect of hepatic impairment on metaxalone pharmacokinetics is unknown; however, metaxalone undergoes expensive hepatic metabolism [see Clinical Pharmacology (12.3)].

8.7 Renal Impairment

Metaxalone tablets are contraindicated in patients with severe renal impairment. Metaxalone tablets should be used with caution and additional follow-up should be considered in patients with mild to moderate renal impairment. The effect of renal impairment on metaxalone pharmacokinetics is unknown; however, metaxalone undergoes renal excretion as unidentified metabolites [see Clinical Pharmacology (12.3)].

10 OVERDOSAGE

Clinical Presentation of Metaxalone Overdose

Deaths by deliberate or accidental overdose have occurred with metaxalone, particularly in combination with other CNS depressants (including alcohol). CNS manifestations may include CNS depression, agitation, hallucinations, delusions, seizures, respiratory depression, and coma. Cardiovascular effects may include tachycardia and hypertension; hypotension has also been reported. Serotonin syndrome, leading to muscle rigidity, tremor, and hyperthermia, has been reported [see Warnings and Precautions (5.1), Drug Interactions (7.1, 7.2)].

Treatment of Metaxalone Overdose

The standard of treatment is supportive care. Monitor for CNS and respiratory depression and manage airway with oxygen as needed. Gastrointestinal decontamination procedures (including emesis) should generally be avoided because aspiration may result from CNS depression and seizures. Extracorporeal elimination such as hemodialysis or plasmapheresis have no proven clinical benefit.

Consider contacting the Poison Help line (1-800-222-1222) or a medical toxicologist for additional overdose management recommendations.

11 DESCRIPTION

Metaxalone tablets, USP contain 800 mg of metaxalone, USP and the following inactive ingredients: alginic acid, ammonium alginate, calcium alginate, corn starch, magnesium stearate and pregelatinized starch (starch 1500 partially pregelatinized maize starch).

Metaxalone tablets, USP is a muscle relaxant for oral administration.

Chemically, metaxalone is 5-[(3,5-dimethylphenoxy) methyl]-2-oxazolidinone. The molecular formula is C12H15NO3, which corresponds to a molecular weight of 221.25. The structural formula is:

Metaxalone, USP is a white to almost white, odorless crystalline powder freely soluble in chloroform, soluble in methanol and in 96% ethanol, but practically insoluble in ether or water.

Meets USP dissolution test 2.

12 CLINICAL PHARMACOLOGY

12.1 Mechanism of Action

Metaxalone’s mechanism of action has not been fully characterized, but may be related to its sedative properties. Metaxalone has no direct action on the contractile mechanism of striated muscle, the motor end plate, or the nerve fiber.

12.2 Pharmacodynamics

The exposure-response relationship and time course of pharmacodynamic response for the safety and effectiveness of metaxalone not been fully characterized.

12.3 Pharmacokinetics

Metaxalone pharmacokinetics were evaluated in two groups of healthy volunteers that received a single oral dose of 800 mg of metaxalone tablets or 400 mg of metaxalone tablets (0.5 times the approved recommended dose). Metaxalone pharmacokinetic parameters are presented below as mean (% CV) unless otherwise specified. Observed metaxalone peak plasma concentrations (Cmax) and area under the curve (AUC) are shown in Table 1. Doubling the dose of metaxalone tablets from 400 mg (0.5 times the approved recommended dose) to 800 mg resulted in a proportional increase in metaxalone Cmaxand AUC.

Table 1: Metaxalone Exposure after a Single-Dose of Metaxalone Tablets Under Fasting Conditions
Dose | Cmax^2 | AUC∞^2
400 mg^1 | 983 (53) ng/mL | 7,479 (51) ng∙h/mL
800 mg | 1,816 (43) ng/mL | 15,044 (46) ng∙h/mL
^10.5 times the approved recommended dose
^2Mean (% CV)

Absorption

The absolute bioavailability of metaxalone is not known. Peak plasma metaxalone concentrations occurred at a mean Tmaxof 3.3 hours (1.5 – 5 hours) of metaxalone tablets under fasted conditions.

The single-dose pharmacokinetic parameters of metaxalone in two groups of healthy volunteers who received 400 mg or 800 mg of metaxalone tablets are shown in Table 1.

Effect of Food:Peak plasma metaxalone concentrations were noted at a mean Tmaxof 4.3 hours (1.5 – 12 hours) under fed conditions. The mean Tmaxunder fasting and fed conditions was 3.3 and 4.3 hours, respectively. Metaxalone exposure was increased and the half-life (t1/2) was decreased following metaxalone tablets administration with a high fat meal as shown in Table 2. The increase in metaxalone exposure coinciding with a reduction in half-life may be attributed to more complete absorption of metaxalone in the presence of a high fat meal.

Table 2: Relative Changes in Metaxalone Exposure, Tmax, and t1/2Following Metaxalone Tablets Administration with a High Fat Meal Compared to Fasting
Dose; (mg) | Cmax; (ng/mL) | AUC 0-t; (ng∙h/mL) | AUC 0-INF; (ng∙h/mL) | Tmax; (hrs) | t 1/2; (hrs)
400 mg* | ↑ 78% | ↑ 24% | ↑ 15% | ↑ 30% | ↓ 73%
800 mg | ↑ 94% | ↑ 46% | ↑ 42% | ↑ 63% | ↓ 48%
*0.5 times the approved recommended dose.

Distribution

Metaxalone apparent volume of distribution is approximately 800 Liters; however, plasma protein binding is unknown.

Elimination

Metaxalone mean ± SD terminal t1/2is 9 ± 4.8 hours and apparent clearance is approximately 67 ± 34 L/h under fasted conditions.

Metabolism:Metaxalone is primarily metabolized by CYP1A2, CYP2D6, CYP2E1, and CYP3A4 and, to a lesser extent, CYP2C8, CYP2C9, and CYP2C19.

Excretion:Metaxalone is metabolized by the liver and excreted in the urine as unidentified metabolites.

Specific Populations

The effect of renal impairment and hepatic impairment on metaxalone pharmacokinetics is unknown [see Use in Specific Populations (8.6, 8.7)] .

Geriatric Patients:The effects of age on the pharmacokinetics of metaxalone were determined following administration of 800 mg of metaxalone tablets under fasted and fed conditions. Age had a significantly greater effect on metaxalone pharmacokinetics under fasted conditions than under fed conditions. Bioavailability under fasted conditions increased with age. Metaxalone bioavailability under fasted and fed conditions in the three groups of healthy volunteers of varying age is shown in Table 3.

Table 3: Metaxalone Pharmacokinetic Parameters under Fasted and Fed Conditions in Three Age Groups Following Oral Administration of 800 mg of metaxalone tablets
Mean Age in Years (± SD) | 26 ± 9 Years Old |  | 39 ± 11 Years Old |  | 72 ± 5 Years Old
Fasted vs. Fed State | Fasted | Fed | Fasted | Fed | Fasted | Fed
Cmax(ng/mL)^1 | 1816 (43) | 3510 (41) | 2719 (46) | 2915 (55) | 3168 (43) | 3680 (59)
Tmax(hours)^1 | 3 (39) | 4.9 (4.8) | 3 (40) | 8.7 (91) | 2.6 (30) | 6.5 (67)
AUC0-t (ng∙h/mL)^1 | 14531 (47) | 20683 (41) | 19836 (40) | 20482 (37) | 23797 (45) | 24340 (48)
AUC∞ (ng∙h/mL)^1 | 15045 (46) | 20833 (41) | 20490 (39) | 20815 (37) | 24194 (44) | 24704 (47)
^1Mean values (% CV)

Male and Female Patients:The exposure of metaxalone was significantly higher in females compared to males as evidenced by Cmax. (2115 ng/mL versus1335 ng/mL) and AUC ∞ (17884 ng∙h/mL versus10328 ng∙h/mL) following administration of 800 mg of metaxalone tablets under fasted conditions. The mean half-life was 11.1 hours in females and 7.6 hours in males. The apparent volume of distribution of metaxalone was approximately 22% higher in males than in females.

Drug Interaction Studies

In Vitro Studies:Metaxalone does not inhibit CYP1A2, CYP2A6, CYP2B6, CYP2C8, CYP2C9, CYP2C19, CYP2D6, CYP2E1, and CYP3A4. Metaxalone does not induce CYP1A2, CYP2B6, and CYP3A4.

13 NONCLINICAL TOXICOLOGY

13.1 Carcinogenesis, Mutagenesis, Impairment of Fertility

Long-term studies to evaluate the carcinogenic potential of metaxalone have not been conducted. Studies to evaluate the mutagenic potential of metaxalone have not been conducted. No effects on fertility were observed in rats administered metaxalone.

16 HOW SUPPLIED/STORAGE AND HANDLING

Metaxalone tablets, USP are available as 800 mg capsule-shaped, scored white to off-white tablet, inscribed with “ 31 90” on the scored side and “ WPI” on the other side. Metaxalone tablets USP, 800 mg has functional scoring.

Bottles of 12 NDC 85766-011-12 (repackaged from NDC 0591-2341-01)

Bottles of 15 NDC 85766-011-15 (repackaged from NDC 0591-2341-01)

Bottles of 20 NDC 85766-011-20 (repackaged from NDC 0591-2341-01)

Bottles of 30 NDC 85766-011-30 (repackaged from NDC 0591-2341-01)

Bottles of 60 NDC 85766-011-60 (repackaged from NDC 0591-2341-01)

Bottles of 90 NDC 85766-011-90 (repackaged from NDC 0591-2341-01)

Bottles of 100 NDC 85766-011-01 (relabeled from NDC 0591-2341-01)

Store at 20° to 25°C (68° to 77°F) [See USP Controlled Room Temperature].

17 PATIENT COUNSELING INFORMATION

Serotonin Syndrome

Inform patients that metaxalone tablets could cause a rare but potentially life-threatening condition called serotonin syndrome. Warn patients of the symptoms of serotonin syndrome and to seek medical attention right away if symptoms develop. Instruct patients to inform their healthcare providers if they are taking, or plan to take, serotonergic drugs [see Warnings and Precautions (5.1) and Drugs Interactions (7.1)].

Central Nervous System Depression

Advise patients that metaxalone tablets may impair mental and/or physical abilities required for performance of hazardous tasks, such as operating machinery or driving a motor vehicle, especially when used with alcohol and other CNS depressants [see Drug Interactions (7.2)].

Distributed by:

Sportpharm LLC

379 Van Ness Ave 1401,

Torrance, CA 90501

Relabeled and Repackaged by:

Enovachem PHARMACEUTICALS

Torrance, CA 90501